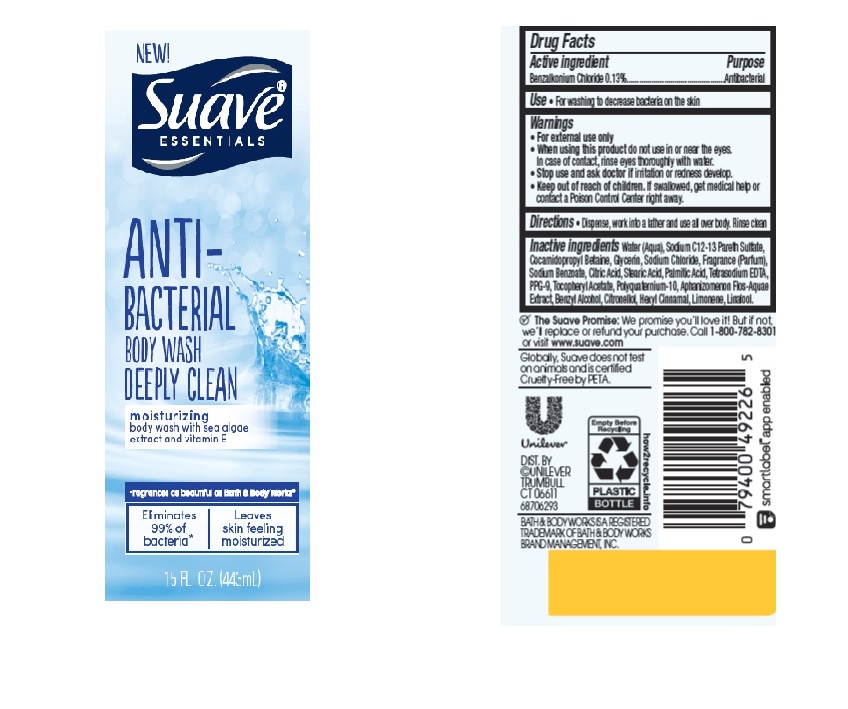 DRUG LABEL: Suave
NDC: 64942-2031 | Form: LIQUID
Manufacturer: Conopco Inc. d/b/a/ Unilever
Category: otc | Type: HUMAN OTC DRUG LABEL
Date: 20220428

ACTIVE INGREDIENTS: BENZALKONIUM CHLORIDE 1.3 mg/1 mL
INACTIVE INGREDIENTS: .ALPHA.-TOCOPHEROL ACETATE; BENZYL ALCOHOL; WATER; GLYCERIN; LIMONENE, (+)-; PALMITIC ACID; STEARIC ACID; SODIUM CHLORIDE; CITRIC ACID MONOHYDRATE; EDETATE SODIUM; .ALPHA.-HEXYLCINNAMALDEHYDE; PPG-9; COCAMIDOPROPYL BETAINE; SODIUM BENZOATE; LINALOOL, (+/-)-; .BETA.-CITRONELLOL, (R)-

Suave Essentials Anti-bacterial Deeply Clean Body Wash

SUAVE ESSENTIALS ANTI-BACTERIAL DEEPLY CLEAN BODY WASH - benzalkonium chloride liquid

Dove Care & Protect Moisture Renew Antibacterial Body Wash

Drug Facts

Active ingredient

Benzalkonium Chloride (0.13%)

Purpose

Antibacterial

Uses

• For washing to decrese bacteria on the skin

Warnings

• For external use only
• When using this product do not use in or near the eyes. In case of contact, rinse eyes thoroughly with wate r
• Stop use and ask doctor if rash or irritation occurs

• Keep out of reach of children except under adult supervision.

If swallowed, get medical help or contact a poison control Center right away.

Directions

Dispense, work into a lather and use all over body. Rinse clean

Inactive ingredients

Water (Aqua), Sodium C12-13 Pareth Sulfate, Cocamidopropyl Betaine, Glycerin, Sodium Chloride, Fragrance (Parfum), Sodium Benzoate, Citric Acid, Stearic Acid, Palmitic Acid, Tetrasodium EDTA, PPG-9, Tocopheryl Acetate, Polyquaternium-10, Aphanizomenon Flos-Aquae Extract, Benzyl Alcohol, Citronellol, Hexyl Cinnamal, Limonene, Linalool.

Questions?

Call 1-800-782-8301